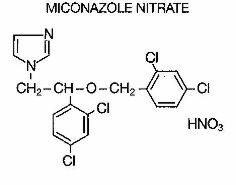 DRUG LABEL: Unknown
Manufacturer: ORTHO PHARMACEUTICAL CORPORATION
Category: prescription | Type: HUMAN PRESCRIPTION DRUG LABELING
Date: 20061231

MONISTAT 3™ (miconazole nitrate, 200 mg)
Vaginal Suppositories

DESCRIPTION

MONISTAT 3 Vaginal Suppositories are white to off-white suppositories, each containing the antifungal agent, miconazole nitrate, 1-[2,4-Dichloro-β-[(2,4-dichlorobenzyl)oxy]phenethyl]-imidazole mononitrate, 200 mg, in a hydrogenated vegetable oil base. Miconazole nitrate for vaginal use is also available as MONISTAT 7 Vaginal Cream and MONISTAT 7 Vaginal Suppositories.

CLINICAL PHARMACOLOGY

Miconazole nitrate exhibits fungicidal activity in vitro against species of the genus Candida. The pharmacologic mode of action is unknown. Following intravaginal administration of miconazole nitrate, small amounts are absorbed. Administration of a single dose of miconazole nitrate suppositories (100 mg) to healthy subjects resulted in a total recovery from the urine and feces of 0.85% (± 0.43%) of the administered dose.

Animal studies indicate that the drug crossed the placenta and doses above those used in humans result in embryo- and fetotoxicity (80 mg/kg, orally), although this has not been reported in human subjects (See PRECAUTIONS).

In multi-center clinical trials in 440 women with vulvovaginal candidiasis, the efficacy of treatment with the MONISTAT 3 Vaginal Suppository for 3 days was compared with treatment for 7 days with MONISTAT 7 Vaginal Cream. The clinical cure rates (free of microbiological evidence and clinical signs and symptoms of candidiasis at 8–10 days and 30–35 days post-therapy) were numerically lower, although statistically different, with the 3-Day Suppository when compared with the 7-Day Cream.

INDICATIONS AND USAGE

MONISTAT 3 Vaginal Suppositories are indicated for the local treatment of vulvovaginal candidiasis (moniliasis). Effectiveness in pregnancy and in diabetic patients has not been established. As MONISTAT is effective only for candidal vulvovaginitis, the diagnosis should be confirmed by KOH smear and/or cultures. Other pathogens commonly associated with vulvovaginitis (Trichomonas and Haemophilus vaginalis [Gardnerella]) should be ruled out by appropriate laboratory methods.

CONTRAINDICATIONS

Patients known to be hypersensitive to this drug.

PRECAUTIONS

General

Discontinue drug if sensitization or irritation is reported during use. The base contained in the suppository formulation may interact with certain latex products, such as that used in vaginal contraceptive diaphragms. Concurrent use is not recommended. MONISTAT 7 Vaginal Cream may be considered for use under these conditions.

Laboratory Tests

If there is a lack of response to MONISTAT 3 Vaginal Suppositories, appropriate microbiological studies (standard KOH smear and/or cultures) should be repeated to confirm the diagnosis and rule out other pathogens.

Carcinogenesis, Mutagenesis, Impairment of Fertility

Long-term animal studies to determine carcinogenic potential have not been performed.

Fertility (Reproduction)

Oral administration of miconazole nitrate in rats has been reported to produce prolonged gestation. However, this effect was not observed in oral rabbit studies. In addition, signs of fetal and embryo toxicity were reported in rat and rabbit studies, and dystocia was reported in rat studies after oral doses at and above 80 mg per kg. Intravaginal administration did not produce these effects in rats.

Pregnancy

Since imidazoles are absorbed in small amounts from the human vagina, they should not be used in the first trimester of pregnancy unless the physician considers it essential to the welfare of the patient.

Clinical studies, during which miconazole nitrate vaginal cream and suppositories were used for up to 14 days, were reported to include 514 pregnant patients. Follow-up reports available in 471 of these patients reveal no adverse effects or complications attributable to miconazole nitrate therapy in infants born to these women.

Nursing Mothers

It is not known whether miconazole nitrate is excreted in human milk. Because many drugs are excreted in human milk, caution should be exercised when miconazole nitrate is administered to a nursing woman.

ADVERSE REACTIONS

During clinical studies with MONISTAT 3 Vaginal Suppository (miconazole nitrate, 200 mg) 301 patients were treated. The incidence of vulvovaginal burning, itching or irritation was 2%. Complaints of cramping (2%) and headaches (1.3%) were also reported. Other complaints (hives, skin rash) occurred with less than a 0.5% incidence. The therapy-related dropout rate was 0.3%.

OVERDOSE

Overdosage of miconazole nitrate in humans has not been reported to date. In mice, rats, guinea pigs and dogs, the oral LD 50 values were found to be 578.1, > 640, 275.9 and > 160 mg/kg, respectively.

DOSAGE AND ADMINISTRATION

MONISTAT 3 Vaginal Suppositories: One suppository (miconazole nitrate, 200 mg) is inserted intravaginally once daily at bedtime for three consecutive days. Before prescribing another course of therapy, the diagnosis should be reconfirmed by smears and/or cultures to rule out other pathogens.

HOW SUPPLIED

MONISTAT 3 Suppositories (miconazole nitrate, 200 mg) are available as 2.5 gm elliptically shaped white to off-white suppositories in packages of three (NDC 0062-5437-01) with a vaginal applicator. Store at 59–86°F (15–30°C).

ORTHO PHARMACEUTICAL CORPORATION
Raritan, New Jersey 08869

© OPC 1984
PRINTED IN USA
REV OCT. 1996
643-10-353-5